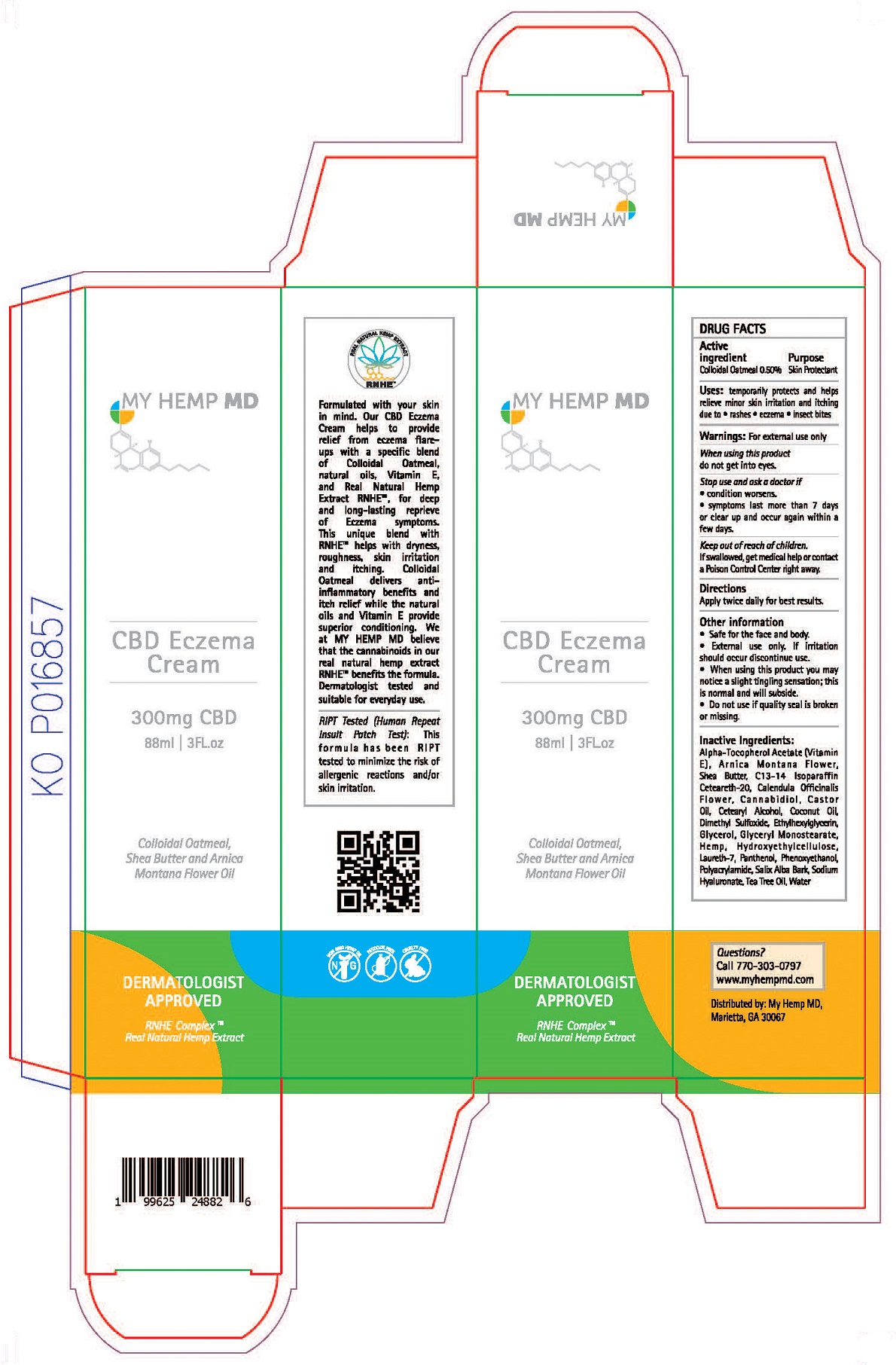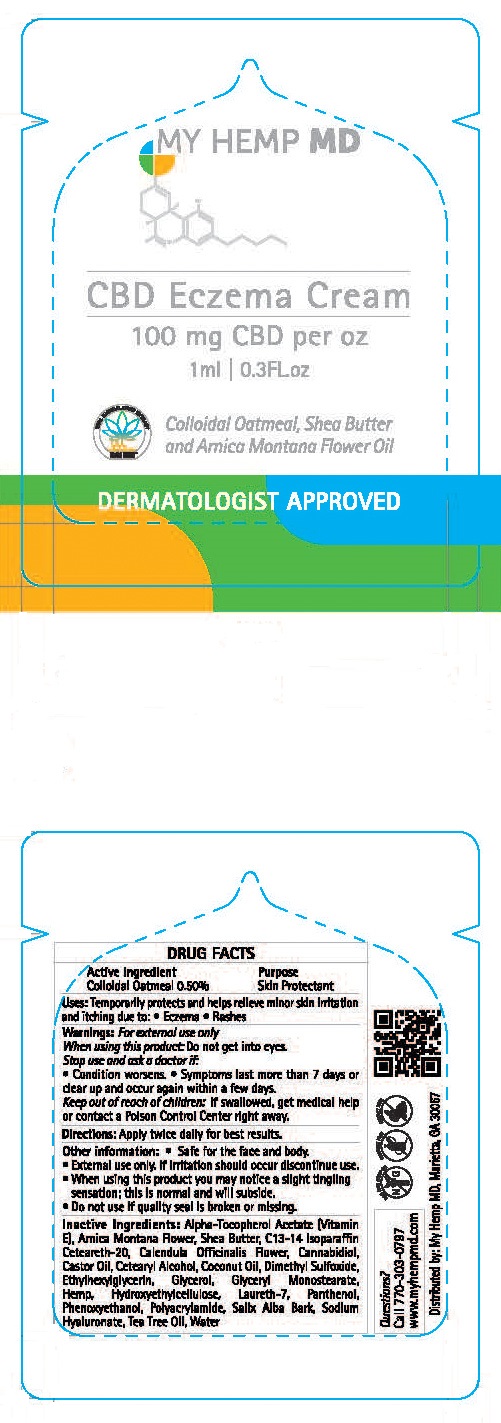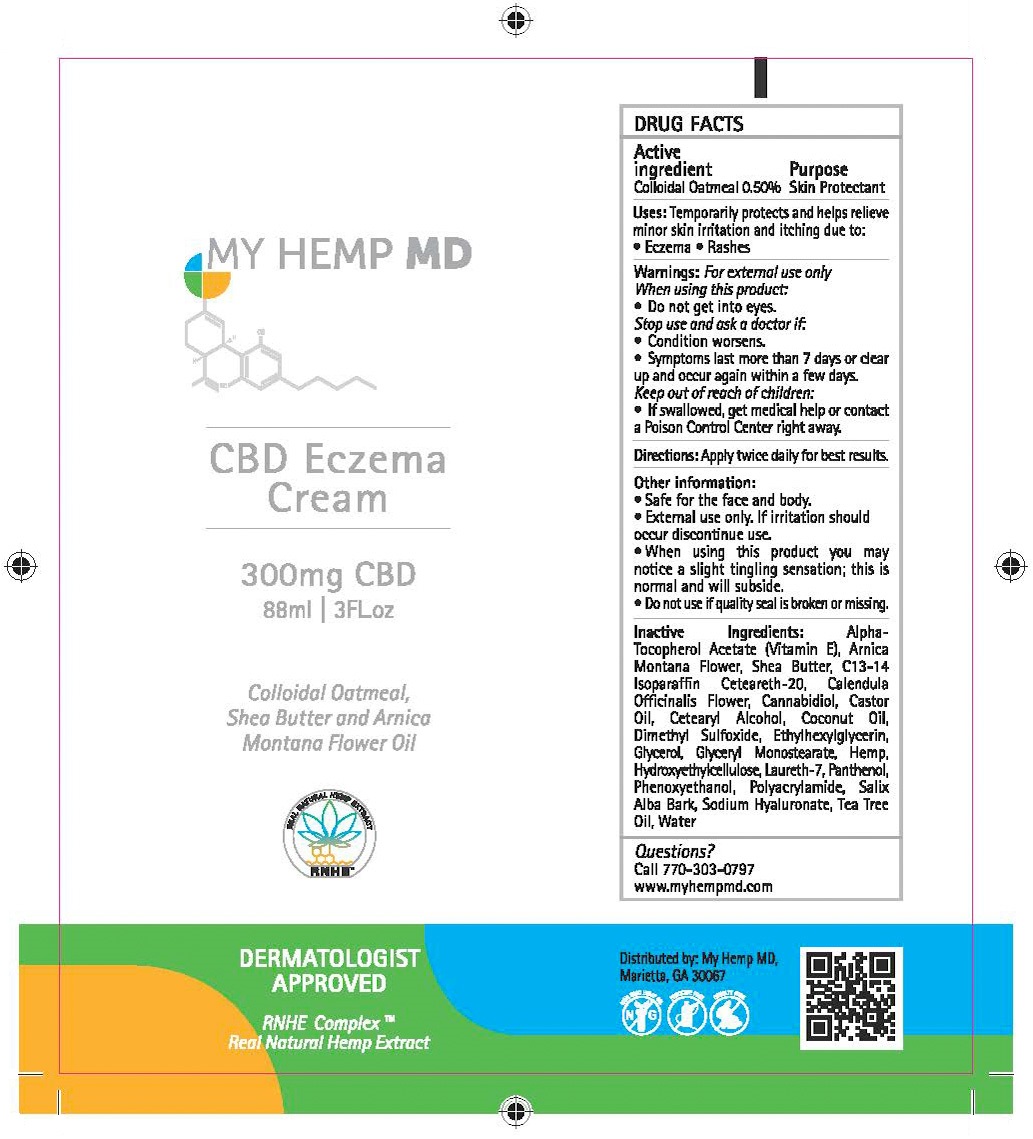 DRUG LABEL: My Hemp MD
NDC: 52261-5200 | Form: CREAM
Manufacturer: Cosco International, Inc.
Category: otc | Type: HUMAN OTC DRUG LABEL
Date: 20200326

ACTIVE INGREDIENTS: OATMEAL 0.005 kg/1 kg
INACTIVE INGREDIENTS: WATER; HYDROXYETHYL CELLULOSE, UNSPECIFIED; GLYCERIN; HYALURONATE SODIUM; PANTHENOL; CALENDULA OFFICINALIS FLOWER; SALIX ALBA BARK; DIMETHYL SULFOXIDE; GLYCERYL MONOSTEARATE; CETOSTEARYL ALCOHOL; POLYOXYL 20 CETOSTEARYL ETHER; SHEA BUTTER; COCONUT OIL; ARNICA MONTANA FLOWER; CASTOR OIL; TEA TREE OIL; .ALPHA.-TOCOPHEROL, D-; HEMP; CANNABIDIOL; LAURETH-7; POLYACRYLAMIDE (1500 MW); C13-14 ISOPARAFFIN; PHENOXYETHANOL; ETHYLHEXYLGLYCERIN

Drug Facts

Active Ingredient.................Purpose

Colloidal Oatmeal 0.50%.........Skin Protectant

PURPOSE

Skin Protectant

INDICATIONS AND USAGE

Uses: Temporarily protects and helps relieve minor skin irratation and itching due to:

- Eczema
- Rashes

Warnings:

For external use only

When using this product:

- Do not get into eyes.

Stop use and ask doctor if:

- Condition worsens.
- Symptoms last more than 7 days or clear up and occur again with a few days.

Keep out of reach of children:

- If swallowed, get medical help or contact a Poison Control Center right away

Directions:

Apply twice daily for best results.

Other information:

- Safe for the face and body
- External use only. If irritation should occur discontinue use.
- When using this product you may notice a slight tingling sensation; this is normal and will subside.
- Do not use if quality seal is broken or missing.

Inactive Ingredients:

Alpha-Tocopherol Acetate (Vitamin E), Arnica Montana Flower Oil, Butyrospermum Parkii (Shea) Butter, C13-14 Isoparaffin, Ceteareth-20, Calendula Officinalis Flower, Cannabidiol, Castor Oil, Cetearyl Alcohol, Coconut Oil, Dimethyl Sulfoxide, Ethylhexylglycerin, Glycerol, Glyceryl Monostearate, Hemp, Hydroxyethylcellulose, Laureth-7, Panthenol, Phenoxyethanol, Polyacrylamide, Salix Alba Bark, Sodium Hyaluronate, Tea Tree Oil, Water

Questions?

Call 770-303-0797

www.myhempmd.com

Distributed by: My Hemp MD

Marietta, GA 30067